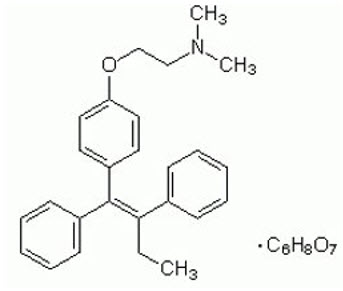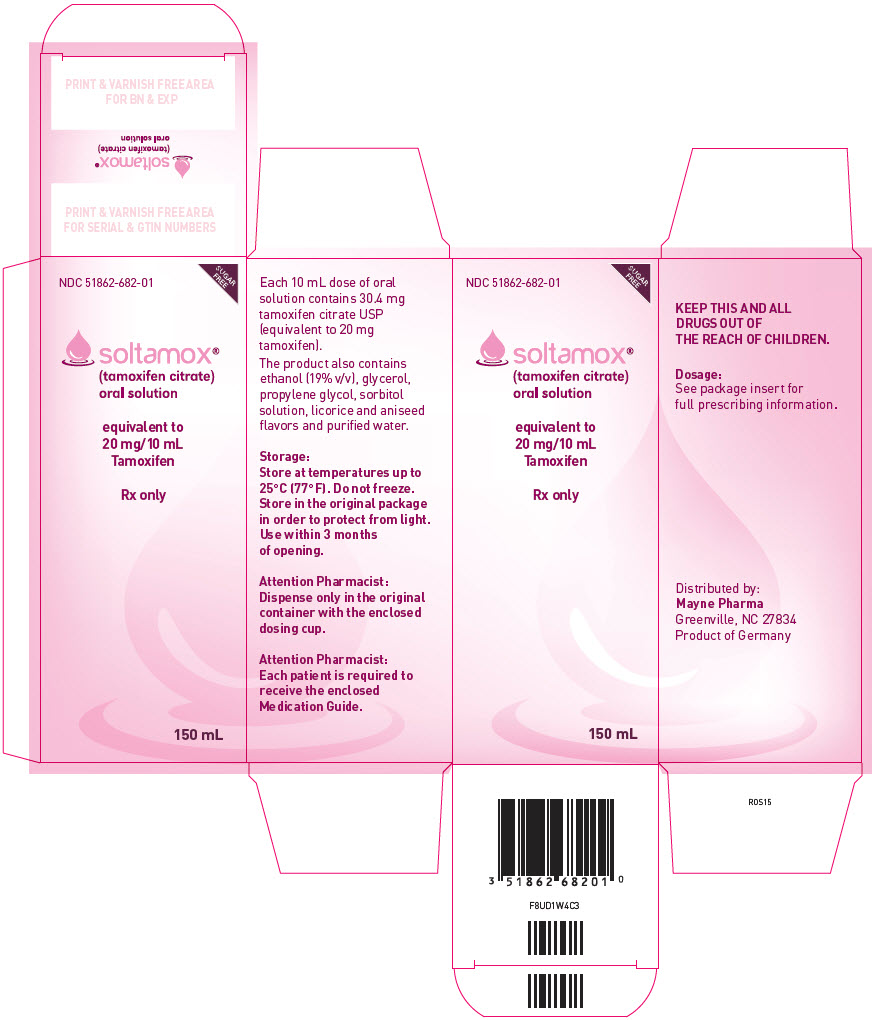 DRUG LABEL: SOLTAMOX
NDC: 51862-682 | Form: LIQUID
Manufacturer: Mayne Pharma
Category: prescription | Type: HUMAN PRESCRIPTION DRUG LABEL
Date: 20211129

ACTIVE INGREDIENTS: TAMOXIFEN CITRATE 20 mg/10 mL
INACTIVE INGREDIENTS: ALCOHOL; GLYCERIN; PROPYLENE GLYCOL; SORBITOL; LICORICE; ANISE; WATER

HIGHLIGHTS OF PRESCRIBING INFORMATION

These highlights do not include all the information needed to use SOLTAMOX® safely and effectively. See full prescribing information for SOLTAMOX®.
SOLTAMOX® (tamoxifen citrate) oral solution
Initial U.S. Approval: 1977

WARNING: UTERINE MALIGNANCIES and THROMBOEMBOLIC EVENTS

See full prescribing information for complete boxed warning.

- Serious, life-threatening, and fatal events from use of tamoxifen include uterine malignancies, stroke, and pulmonary embolism. (5.1, 5.2)
- Discuss risks and benefits of tamoxifen with women at high risk for breast cancer and women with ductal carcinoma in situ (DCIS) when considering tamoxifen use to reduce the risk of developing breast cancer. (5.1, 5.2)
- For most patients already diagnosed with breast cancer, the benefits of tamoxifen outweigh its risks. (5.1, 5.2)

1 INDICATIONS AND USAGE

SOLTAMOX is an estrogen agonist/antagonist indicated:

- For treatment of adult patients with estrogen receptor-positive metastatic breast cancer (1.1)
- For adjuvant treatment of adult patients with early stage estrogen receptor- positive breast cancer (1.2)
- To reduce risk of invasive breast cancer following breast surgery and radiation in adult women with ductal carcinoma in situ (DCIS) (1.3)
- To reduce the incidence of breast cancer in adult women at high risk (1.4)

2 DOSAGE AND ADMINISTRATION

- Metastatic breast cancer: 20-40 mg per day. For doses greater than 20 mg per day, administer in divided doses (morning and evening). (2)
- Adjuvant treatment of breast cancer, DCIS, reduction of breast cancer incidence in women at high risk: 20 mg per day (2)

3 DOSAGE FORMS AND STRENGTHS

- Oral solution: Each 10 mL of solution contains 20 mg tamoxifen, equivalent to 30.4 mg tamoxifen citrate. (3)

4 CONTRAINDICATIONS

- Known hypersensitivity to tamoxifen or any other SOLTAMOX ingredient (4)
- In patients who require concomitant warfarin therapy or have a history of deep vein thrombosis or pulmonary embolus, if the indication for treatment is either reduction of breast cancer incidence in high-risk patients or risk reduction of invasive breast cancer after treatment of DCIS (4)

5 WARNINGS AND PRECAUTIONS

- Uterine malignancies: Promptly evaluate abnormal vaginal bleeding in a woman with current or past tamoxifen use. (5.1)
- Thromboembolic events: Risk increases with coadministered chemotherapy. For treatment of breast cancer, consider risks and benefits in patients with a history of thromboembolic events. (5.2)
- Embryo-fetal toxicity: Can cause fetal harm. Advise females of reproductive potential of the potential risk to a fetus and to use effective contraception. (5.3, 8.1, 8.3)
- Effects on the liver: Liver cancer and liver abnormalities, some fatal, have occurred. Perform periodic liver function testing. (5.4, 5.9)

6 ADVERSE REACTIONS

Most common adverse reactions: hot flashes, mood disturbances, vaginal discharge, vaginal bleeding, nausea, and fluid retention (6.1).

To report SUSPECTED ADVERSE REACTIONS, contact Mayne Pharma at 1-844-825-8500 or FDA at 1-800-FDA-1088 or www.fda.gov/medwatch.

7 DRUG INTERACTIONS

- Anastrozole and letrozole: Should not be used in combination with tamoxifen. (7.1)
- Warfarin: Do not use in patients taking tamoxifen for DCIS and for reduction in breast cancer incidence in women at high risk. (4) Closely monitor coagulation indices for increased anticoagulant effect when used with tamoxifen for metastatic breast cancer or as adjuvant therapy. (7.2)

8 USE IN SPECIFIC POPULATIONS

- Lactation: Advise not to breastfeed. (8.2)
- Females and males of reproductive potential: Verify pregnancy status of females prior to initiation of tamoxifen. Advise females to use effective contraception. (8.3)

FULL PRESCRIBING INFORMATION

WARNING: UTERINE MALIGNANCIES and THROMBOEMBOLIC EVENTS

Serious and life-threatening events from the use of SOLTAMOX include uterine malignancies, stroke, and pulmonary embolism [see Warnings and Precautions (5.1, 5.2)]. Fatal cases of each type of event have occurred.

Incidence rates per 1000 women-years for these events were estimated from the National Surgical Adjuvant Breast and Bowel Project (NSABP) P-1 trial in women at high risk for breast cancer [see Clinical Studies (14.4)]:

- Endometrial adenocarcinoma: 2.20 for tamoxifen vs. 0.71 for placebo
- Uterine sarcoma: 0.17 for tamoxifen vs. 0.04 for placebo
- Stroke: 1.43 for tamoxifen vs. 1.00 for placebo.
- Pulmonary embolism: 0.75 for tamoxifen versus 0.25 for placebo.

Discuss the potential benefits of tamoxifen versus the potential risks of these serious events with women at high risk for breast cancer and women with ductal carcinoma in situ (DCIS) considering tamoxifen to reduce the risk of developing breast cancer [see Warnings and Precautions (5)]. For most patients already diagnosed with breast cancer, the benefits of tamoxifen outweigh its risks.

1 INDICATIONS AND USAGE

1.1 Metastatic Breast Cancer

SOLTAMOX is indicated for the treatment of adult patients with estrogen receptor-positive metastatic breast cancer.

1.2 Adjuvant Treatment of Breast Cancer

SOLTAMOX is indicated:

- for the adjuvant treatment of adult patients with early stage estrogen receptor-positive breast cancer
- to reduce the occurrence of contralateral breast cancer in adult patients when used as adjuvant therapy for the treatment of breast cancer.

1.3 Ductal Carcinoma in Situ

In adult women with DCIS, following breast surgery and radiation, SOLTAMOX is indicated to reduce the risk of invasive breast cancer [see Boxed Warning and Clinical Studies (14.3)].

1.4 Reduction in Breast Cancer Incidence in Women at High Risk

SOLTAMOX is indicated to reduce the incidence of breast cancer in adult women at high risk for breast cancer. [see Boxed Warning and Clinical Studies (14.4)].

2 DOSAGE AND ADMINISTRATION

Metastatic Breast Cancer

For patients with breast cancer, the recommended daily dose of SOLTAMOX is 20 to 40 mg. Doses greater than 20 mg per day should be given in divided doses (morning and evening).

Adjuvant Treatment of Breast Cancer

For use in the adjuvant setting, the recommended dose of SOLTAMOX is 20 mg daily for 5-10 years [see Clinical Studies (14.2)]. Doses greater than 20 mg daily yield no additional clinical benefit.

Ductal Carcinoma in Situ

For patients with DCIS, the recommended dose of SOLTAMOX is 20 mg daily for 5 years.

Reduction in Breast Cancer Incidence in Women at High Risk

In the risk reduction setting, the recommended dose of SOLTAMOX is 20 mg daily for 5 years.

3 DOSAGE FORMS AND STRENGTHS

SOLTAMOX oral solution: Each 10 mL of solution contains 20 mg tamoxifen, equivalent to 30.4 mg tamoxifen citrate.

4 CONTRAINDICATIONS

- SOLTAMOX is contraindicated in patients with known hypersensitivity (e.g., angioedema, serious skin reactions) to tamoxifen or any other SOLTAMOX ingredient [see Adverse Reactions (6.2)].
- SOLTAMOX is contraindicated in patients who require concomitant warfarin therapy or have a history of deep vein thrombosis or pulmonary embolus if the indication for treatment is either reduction of breast cancer incidence in high-risk patients or risk reduction of invasive breast cancer after treatment of DCIS [see Warnings and Precautions (5.2) and Drug Interactions (7.2)].

5 WARNINGS AND PRECAUTIONS

5.1 Endometrial Cancer, Uterine Sarcoma, and Other Effects on the Uterus

Endometrial Cancer and Uterine Sarcoma

An increased incidence of uterine malignancies (endometrial adenocarcinoma and uterine sarcoma), including fatal cases, has been reported with tamoxifen treatment. The underlying mechanism is unknown, but may be related to the estrogen-like effect of tamoxifen. Most uterine malignancies seen with tamoxifen are classified as adenocarcinoma of the endometrium; however, uterine sarcomas, including malignant mixed mullerian tumors (MMMT), have also been reported. Uterine sarcoma was generally associated with a higher FIGO stage (III/IV) at diagnosis, poor prognosis, and short survival. Uterine sarcoma has been reported to occur more frequently among long-term users (≥2 years) of tamoxifen than non-users.

Promptly evaluate any patient receiving or who has previously received tamoxifen who reports abnormal vaginal bleeding. Patients receiving or who have previously received tamoxifen should have annual gynecological examinations. Advise patients to promptly inform a healthcare provider if they experience any abnormal gynecological symptoms (e.g., menstrual irregularities, abnormal vaginal bleeding, changes in vaginal discharge, or pelvic pain or pressure). There are no data to suggest that routine endometrial sampling in asymptomatic women taking tamoxifen is beneficial.

In a review of long-term data (median length of total follow-up was 6.9 years, including blinded follow-up) on 8,306 women with an intact uterus at randomization in the NSABP P-1 risk reduction trial, the incidence of both adenocarcinomas and uterine sarcomas was increased in women taking tamoxifen.

- During blinded follow-up, there were 36 cases of FIGO Stage I endometrial adenocarcinoma (22 were FIGO Stage IA, 13 IB, and 1 IC) in women receiving tamoxifen and 15 cases in women receiving placebo [14 were FIGO Stage I (9 IA and 5 IB), and 1 case was FIGO Stage IV].
- During total follow-up, endometrial adenocarcinoma was reported in 53 women randomized to tamoxifen (30 cases of FIGO Stage IA, 20 were Stage IB, 1 was Stage IC, and 2 were Stage IIIC), and 17 women randomized to placebo (9 cases were FIGO Stage IA, 6 were Stage IB, 1 was Stage IIIC, and 1 was Stage IVB) (incidence per 1,000 women-years of 2.20 and 0.71, respectively).
- Uterine sarcomas were reported in 4 women randomized to tamoxifen (1 was FIGO IA, 1 was FIGO IB, 1 was FIGO IIA, and 1 was FIGO IIIC) and 1 patient randomized to placebo (FIGO IA); incidence per 1,000 women-years of 0.17 and 0.04, respectively. Of the patients randomized to tamoxifen, the FIGO IA and IB cases were a MMMT and sarcoma, respectively; the FIGO II was a MMMT; and the FIGO III was a sarcoma; and the 1 patient randomized to placebo had a MMMT.
- A similar increased incidence in endometrial adenocarcinoma and uterine sarcoma was observed among women receiving tamoxifen in 5 other NSABP clinical trials.

In the NSABP P-1 trial, endometrial sampling did not alter the endometrial cancer detection rate compared to women who did not undergo endometrial sampling (0.6% with sampling, 0.5% without sampling) for women who had not undergone hysterectomy.

Non-Malignant Effects on the Uterus

An increased incidence of endometrial changes including hyperplasia and polyps has been reported with tamoxifen treatment. The incidence and pattern of this increase suggest that the underlying mechanism is related to the partial estrogenic effect of tamoxifen. There have been reports of endometriosis and uterine fibroids in women receiving tamoxifen. Ovarian cysts have also been observed in premenopausal patients with advanced breast cancer who have been treated with tamoxifen. Tamoxifen has been reported to cause menstrual irregularity or amenorrhea.

5.2 Thromboembolic Events

There is an increased incidence of thromboembolic events, including deep vein thrombosis and pulmonary embolism, during tamoxifen therapy. When tamoxifen is coadministered with chemotherapy, there is a further increase in the risk of thromboembolic events.

For treatment of breast cancer, carefully consider the risks and benefits of tamoxifen in women with a history of thromboembolic events. For women with DCIS and for the reduction in breast cancer incidence in women at high risk, tamoxifen is contraindicated in women who require concomitant warfarin-type anticoagulant therapy or in women with a history of deep vein thrombosis or pulmonary embolus. Advise patients to seek medical attention immediately if signs or symptoms of a thromboembolic event occur.

Data from the NSABP P-1 trial in women at high risk for breast cancer show that participants receiving tamoxifen without a history of pulmonary emboli (PE) had a statistically significant increase in pulmonary emboli (events: 18 tamoxifen, 6 placebo; incidence rate per 1,000 women-years: 0.75 tamoxifen versus 0.25 placebo; RR = 3.01, 95% CI: 1.15 to 9.27) [see Clinical Studies (14.4)]. Three of the pulmonary emboli, all in the tamoxifen arm, were fatal. Eighty-seven percent of the cases of pulmonary embolism occurred in women at least 50 years of age at randomization. Among women receiving tamoxifen, PE events occurred between 2 and 60 months (average = 27 months) from the start of treatment.

In this same population, a non-statistically significant increase in deep vein thrombosis (DVT) was seen in the tamoxifen group (30 tamoxifen, 19 placebo; relative risk (RR) = 1.59, 95% CI: 0.86 to 2.98). The same increase in relative risk was seen in women ≤49 and in women ≥50, although fewer events occurred in younger women. Women with thromboembolic events were at risk for a second related event (7 out of 25 women on placebo, 5 out of 48 women on tamoxifen) and were at risk for thromboembolic event and treatment related complications (0/25 on placebo, 4/48 on tamoxifen). Among women receiving tamoxifen, DVT events occurred between 2 and 57 months (average = 19 months) from the start of treatment.

In a small substudy (N = 81) of the NSABP-1 trial, there appeared to be no benefit to screening women for Factor V Leiden and Prothrombin mutations G20210A as a means to identify those who may not be appropriate candidates for tamoxifen therapy.

In the NSABP P-1 trial, there was an increase in stroke among women randomized to tamoxifen compared to women randomized to placebo (events: 24 placebo; 34 tamoxifen; incidence rate per 1,000 women-years: 1.43 tamoxifen versus 1.00 placebo; RR = 1.42, 95% CI: 0.82 to 2.51). Six of the 24 strokes in the placebo group were considered hemorrhagic in origin and 10 of the 34 strokes in the tamoxifen group were categorized as hemorrhagic. Seventeen of the 34 strokes in the tamoxifen group were considered occlusive and 7 were considered to be of unknown etiology. Fourteen of the 24 strokes on the placebo arm were reported to be occlusive and 4 of unknown etiology. Three strokes in the placebo group and 4 strokes in the tamoxifen group were fatal. Eighty-eight percent of the strokes occurred in women at least 50 years of age at the time of randomization. Among women receiving tamoxifen, the stroke events occurred between 1 and 63 months (average = 30 months) from the start of treatment.

5.3 Embryo-Fetal Toxicity

Tamoxifen can cause fetal harm when administered to a pregnant woman. There are postmarketing reports of vaginal bleeding, spontaneous abortions, birth defects, and fetal deaths in pregnant women taking tamoxifen. In a primate model, administration of tamoxifen at doses 2 times the maximum recommended human dose resulted in spontaneous abortion. In rat and rabbit studies, doses of tamoxifen less than or equal to human doses resulted in increased embryotoxicity, abortions, and altered learning behaviors in the offspring. Additionally, rodent models showed reproductive tract changes often associated with diethylstilbestrol (DES) in offspring of both sexes.

Advise pregnant women of the potential risks to a fetus, including the potential long-term risk of a DES-like syndrome. Advise females of reproductive potential to use effective non-hormonal contraception during treatment with tamoxifen and for 2 months following the last dose [see Use in Specific Populations (8.1, 8.3)].

5.4 Liver Cancer and Other Effects on the Liver

Liver Cancer

In the Swedish Breast Cancer Cooperative Group trial using adjuvant tamoxifen 40 mg per day (two times the recommended dosage) for 2 to 5 years, 3 cases of liver cancer were reported in the tamoxifen-treated group versus 1 case in the observation group [see Clinical Studies (14.2)]. One case of liver cancer was reported in NSABP P-1 (women at high risk for breast cancer) in a participant randomized to tamoxifen [see Clinical Studies (14.4)].

Hepatocellular carcinoma has been observed in animals receiving tamoxifen [see Nonclinical Toxicology (13.1)].

Non-Malignant Effects on the Liver

Tamoxifen has been associated with changes in liver enzyme levels, and on rare occasions, a spectrum of more severe liver abnormalities including fatty liver, cholestasis, hepatitis and hepatic necrosis. Some of these serious cases included fatalities. In most reported cases, the relationship to tamoxifen is uncertain. However, some positive rechallenges and dechallenges have been reported. Monitor liver function periodically.

In the NSABP P-1 trial, grade 3 to 4 changes in liver function (SGOT, SGPT, bilirubin, alkaline phosphatase) were observed (10 on placebo and 6 on tamoxifen). Serum lipids were not systematically collected.

5.5 Other Cancers

A number of second primary tumors occurring at sites other than the endometrium have been reported following the treatment of breast cancer with tamoxifen in clinical trials. Data from the NSABP B-14 (adjuvant breast cancer study in women with axillary node-negative breast cancer) and P-1 studies show no increase in other (non-uterine) cancers among patients receiving tamoxifen [see Clinical Studies (14.2, 14.4)]. Whether an increased risk for other (non-uterine) cancers is associated with tamoxifen is still unknown.

5.6 Hypercalcemia in Patients with Metastatic Breast Cancer

As with other additive hormonal therapy (estrogens and androgens), hypercalcemia has been reported in some breast cancer patients with bone metastases within a few weeks of starting treatment with tamoxifen. If hypercalcemia occurs, treat as appropriate; if the hypercalcemia is severe, discontinue tamoxifen.

5.7 Hematologic Effects

Decreases in platelet counts, usually to 50,000-100,000/mm^3, infrequently lower, have been reported in patients taking tamoxifen for breast cancer. In the NSABP P-1 trial, 6 women on tamoxifen and 2 on placebo experienced grade 3 to 4 decreases in platelet counts (≤50,000/mm^3). In patients with significant thrombocytopenia, hemorrhagic episodes have occurred, but it is uncertain if these episodes were due to tamoxifen therapy.

Leukopenia has been observed, sometimes in association with anemia and/or thrombocytopenia. There have been reports of neutropenia and pancytopenia, including some severe cases, in patients receiving tamoxifen. Perform periodic complete blood counts, including platelet counts.

5.8 Effects on the Eye

Ocular disturbances, including corneal changes, decrement in color vision perception, retinal vein thrombosis, and retinopathy have been reported in patients receiving tamoxifen. An increased incidence of cataracts and the need for cataract surgery have also been reported. Patients should be advised to seek medical attention if they experience any visual disturbance.

In the NSABP P-1 trial, an increased risk of borderline significance of developing cataracts among those women without cataracts at baseline (540 tamoxifen; 483 placebo; RR = 1.13, 95% CI: 1.00 to 1.28) was observed. Among these same women, tamoxifen was associated with an increased risk of having cataract surgery (101 tamoxifen; 63 placebo; RR = 1.62, 95% CI: 1.18 to 2.22) [see Clinical Studies (14.4)]. Among all women on the trial (with or without cataracts at baseline), tamoxifen was associated with an increased risk of having cataract surgery (201 tamoxifen; 129 placebo; RR = 1.58, 95% CI: 1.26 to 1.97).

5.9 Laboratory Monitoring

Perform periodic complete blood counts, including platelet counts, and periodic liver function tests during therapy with SOLTAMOX. Periodic monitoring of plasma triglycerides and cholesterol may be indicated in patients with preexisting hyperlipidemias.

6 ADVERSE REACTIONS

The following serious adverse reactions are discussed below and elsewhere in the labeling:

- Uterine malignancies [see Boxed Warning, Warnings and Precautions (5.1), and Clinical Studies (14.4)]
- Thromboembolic events [see Boxed Warning, Warnings and Precautions (5.2), and Clinical Studies (14.4)]
- Embryo-Fetal Toxicity [see Warnings and Precautions (5.3), and Use in Specific Populations (8.1, 8.3)]
- Liver cancer [see Warnings and Precautions (5.4)]

6.1 Clinical Trials Experience

Because clinical trials are conducted under widely varying conditions, adverse reaction rates observed in the clinical trials of a drug cannot be directly compared to rates in the clinical trials of another drug and may not reflect the rates observed in practice.

Adverse Reactions in Patients with Metastatic Breast Cancer

In patients treated with tamoxifen for metastatic breast cancer, the most frequent adverse reaction was hot flashes. Other adverse reactions which were seen less commonly are hypercalcemia, peripheral edema, distaste for food, pruritus vulvae, depression, dizziness, lightheadedness, headache, hair thinning and/or partial hair loss, and vaginal dryness.

Increased bone, tumor pain and local disease flare have occurred. Patients with soft tissue disease may have sudden increases in the size of preexisting lesions, sometimes associated with marked erythema within and surrounding the lesions and/or the development of new lesions. When they occurred, the bone pain or disease flares were seen shortly after starting tamoxifen and generally subsided rapidly.

Premenopausal Women with Metastatic Breast Cancer

Table 1 summarizes the incidence of adverse reactions reported at a frequency of 2% or greater from clinical trials that compared tamoxifen therapy to ovarian ablation in premenopausal patients with metastatic breast cancer.

Table 1: Adverse Reactions (frequency ≥2% in either arm) from Trials Comparing Tamoxifen to Ovarian Ablation in Premenopausal Women with Metastatic Breast Cancer
 | % of Women
 | Tamoxifen N=104 | Ovarian Ablation N=100
Adverse Reactions [Some women had more than one adverse reaction.]
Flush | 33 | 46
Amenorrhea | 16 | 69
Altered menses | 13 | 5
Oligomenorrhea | 9 | 1
Bone pain | 6 | 6
Menstrual disorder | 6 | 4
Nausea | 5 | 4
Cough/coughing | 4 | 1
Edema | 4 | 1
Fatigue | 4 | 1
Musculoskeletal pain | 3 | 0
Pain | 3 | 4
Ovarian cyst(s) | 3 | 2
Depression | 2 | 2
Abdominal cramps | 1 | 2
Anorexia | 1 | 2

Adverse Reactions in Adjuvant Breast Cancer

In the NSABP B-14 study, women with axillary node-negative breast cancer were randomized to 5 years of tamoxifen 20 mg per day or placebo following primary surgery [see Clinical Studies (14.2)]. Table 2 presents the most common adverse reactions (mean follow-up of approximately 6.9 years) that were more common on tamoxifen than placebo.

Table 2: Most Common Adverse Reactions in Women with Axillary Node-Negative Breast Cancer (Study NSABP B-14)
 | % of Women
 | Tamoxifen N=1,422 | Placebo N=1,437
Hot flashes | 64 | 48
Fluid retention | 32 | 30
Vaginal discharge | 30 | 15
Nausea | 26 | 24
Irregular menses | 25 | 19
Weight loss (>5%) | 23 | 18
Skin changes | 19 | 15
Increased SGOT | 5 | 3
Increased bilirubin | 2 | 1
Increased creatinine | 2 | 1
Thrombocytopenia [Defined as a platelet count of < 100,000/mm^3] | 2 | 1
Thrombotic events [Two of the tamoxifen-treated patients who had thrombotic events died.]
Deep vein thrombosis | 0.8 | 0.2
Pulmonary embolism | 0.5 | 0.2
Superficial phlebitis | 0.4 | 0

In the Eastern Cooperative Oncology Group (ECOG) adjuvant breast cancer trial [see Clinical Studies (14.2)], tamoxifen or placebo was administered for 2 years to women following mastectomy. When compared to placebo, tamoxifen showed a higher incidence of hot flashes (19% vs. 8% for placebo). The incidence of all other adverse reactions was similar in the two treatment groups with the exception of thrombocytopenia, where the incidence for tamoxifen was 10% vs. 3% for placebo.

In other adjuvant studies [the Toronto study and Tamoxifen Adjuvant Trial Organization (NATO)], women received either tamoxifen or no therapy [see Clinical Studies (14.2)]. In the Toronto study, hot flashes were observed in 29% of patients for tamoxifen vs. 1% in the untreated group. In the NATO trial, hot flashes and vaginal bleeding were reported in 2.8% and 2.0% of women, respectively, for tamoxifen vs. 0.2% for each in the untreated group.

Anastrozole Adjuvant Trial (ATAC: Arimidex, Tamoxifen, Alone or in Combination) – Study of Anastrozole Compared to Tamoxifen for Adjuvant Treatment of Early Breast Cancer

At a median follow-up of 33 months, the combination of anastrozole and tamoxifen did not demonstrate an efficacy benefit when compared to tamoxifen monotherapy in all patients as well as in the hormone receptor- positive subpopulation. The combination treatment arm was discontinued from the trial. The median duration of adjuvant treatment for safety evaluation was 59.8 months and 59.6 months for patients receiving anastrozole 1 mg and tamoxifen 20 mg monotherapy, respectively.

Adverse reactions occurring with an incidence of at least 5% in either single-drug treatment group during treatment or within 14 days of the end of treatment are presented in Table 3.

Table 3: Adverse Reactions Occurring with an Incidence of at Least 5% in Either Single-Drug Treatment Group During Treatment or Within 14 Days of the End of Treatment in the ATAC Trial
 | % of Women
Body system and adverse reactions by COSTART-preferred term [COSTART: Coding Symbols for Thesaurus of Adverse Reaction Terms. A patient may have had more than 1 adverse reaction, including more than 1 adverse reaction in the same body system.] | Tamoxifen N=3,094 | Anastrozole N=3,092
Body as a whole
Asthenia | 18 | 19
Pain | 16 | 17
Back pain | 10 | 10
Accidental injury | 10 | 10
Abdominal pain | 9 | 9
Infection | 9 | 9
Headache | 8 | 10
Flu syndrome | 6 | 6
Cyst | 5 | 5
Chest pain | 5 | 7
Neoplasm | 5 | 5
Cardiovascular
Vasodilatation | 41 | 36
Hypertension | 11 | 13
Digestive
Nausea | 11 | 11
Constipation | 8 | 8
Diarrhea | 7 | 9
Dyspepsia | 6 | 7
Gastrointestinal disorder | 5 | 7
Hemic and lymphatic
Lymphedema | 11 | 10
Anemia | 5 | 4
Metabolic and nutritional
Peripheral edema | 11 | 10
Weight gain | 9 | 9
Hypercholesterolemia | 3 | 9
Musculoskeletal
Arthritis | 14 | 17
Arthralgia | 11 | 15
Osteoporosis | 7 | 11
Fracture | 7 | 10
Bone pain | 6 | 7
Joint disorder | 5 | 6
Myalgia | 5 | 6
Arthrosis | 5 | 7
Nervous system
Depression | 12 | 13
Insomnia | 9 | 10
Dizziness | 8 | 8
Anxiety | 6 | 6
Paresthesia | 5 | 7
Respiratory
Pharyngitis | 14 | 14
Cough increased | 9 | 8
Dyspnea | 8 | 8
Sinusitis | 5 | 6
Bronchitis | 5 | 5
Skin and appendages
Rash | 13 | 11
Sweating | 6 | 5
Special senses
Cataract specified | 7 | 6
Urogenital
Urinary tract infection | 10 | 8
Leukorrhea | 9 | 3
Vaginal hemorrhage [Vaginal hemorrhage without further diagnosis] | 6 | 4
Breast pain | 6 | 8
Vaginitis | 5 | 4
Vulvovaginitis | 5 | 6
Breast neoplasm | 5 | 5

Certain adverse reactions and combinations of adverse reactions were prospectively specified for analysis in the ATAC trial, based on the known pharmacologic properties and safety profiles of the two drugs (Table 4).

Table 4: Percentage of Patients with Pre-Specified Adverse Reactions in the ATAC Trial [Patients with multiple events in the same category are counted only once in that category.]
 | % of Women |  | Odds Ratio [The odds ratios <1 favor anastrozole and those >1 favor tamoxifen.] | 95% CI
 | Tamoxifen N=3,094 | Anastrozole N=3,092 | Odds Ratio [The odds ratios <1 favor anastrozole and those >1 favor tamoxifen.] | 95% CI
Hot flashes | 41 | 36 | 0.80 | 0.73 to 0.89
Musculoskeletal events [Refers to joint symptoms, including joint disorder, arthritis, arthrosis and arthralgia.] | 29 | 36 | 1.32 | 1.19 to 1.47
Mood disturbances | 18 | 19 | 1.10 | 0.97 to 1.25
Fatigue/asthenia | 18 | 19 | 1.07 | 0.94 to 1.22
Vaginal discharge | 13 | 4 | 0.24 | 0.19 to 0.30
Nausea and vomiting | 12 | 13 | 1.03 | 0.88 to 1.19
Vaginal bleeding | 10 | 5 | 0.50 | 0.41 to 0.61
Cataracts | 7 | 6 | 0.85 | 0.69 to 1.04
All fractures | 7 | 10 | 1.57 | 1.30 to 1.88
Fractures of spine, hip, or wrist | 3 | 4 | 1.48 | 1.13 to 1.95
Wrist/Colles' fractures | 2 | 2
Hip fractures | 1 | 1
Spine fractures | 1 | 1
Venous thromboembolic events | 5 | 3 | 0.61 | 0.47 to 0.80
Deep venous thromboembolic events | 2 | 2 | 0.64 | 0.45 to 0.93
Ischemic cerebrovascular events | 3 | 2 | 0.70 | 0.50 to 0.97
Ischemic cardiovascular disease | 3 | 4 | 1.23 | 0.95 to 1.60
Endometrial cancer [Percentages calculated based upon the numbers of women who had not undergone hysterectomy at baseline.] | 0.6 | 0.2 | 0.31 | 0.10 to 0.94

Adverse Reactions in Ductal Carcinoma in Situ

The types and frequency of adverse reactions in the NSABP B-24 trial in women with DCIS were consistent with those observed in the other adjuvant trials conducted with tamoxifen [see Clinical Studies (14.3)].

Adverse Reactions in Women at High Risk for Breast Cancer

In the NSABP P-1 trial, there was an increase in five serious adverse reactions in the tamoxifen group [see Warnings and Precautions (5.1, 5.2, and 5.8) and Clinical Studies (14.4)]:

- endometrial cancer (33 cases in the tamoxifen group vs. 14 in the placebo group);
- pulmonary embolism (18 cases in the tamoxifen group vs. 6 in the placebo group);
- deep vein thrombosis (30 cases in the tamoxifen group vs. 19 in the placebo group);
- stroke (34 cases in the tamoxifen group vs. 24 in the placebo group);
- cataract formation (540 cases in the tamoxifen group vs. 483 in the placebo group), and
- cataract surgery (101 cases in the tamoxifen group vs. 63 in the placebo group).

Table 5 presents the adverse reactions observed in NSABP P-1 by treatment arm. Only adverse reactions more common on tamoxifen than placebo are shown.

Table 5: Most Common Adverse Reactions in Women at High Risk for Breast Cancer (Study NSABP P-1)
 | % of Women
 | Tamoxifen N=6,681 | Placebo N=6,707
Self-Reported Symptoms | N=6,441 [Number with quality of life questionnaires] | N=6,469
Hot flashes | 80 | 68
Vaginal discharge | 55 | 35
Vaginal bleeding | 23 | 22
Laboratory Abnormalities | N=6,520 [Number with treatment follow-up forms] | N=6,535
Platelets decreased | 0.7 | 0.3
Adverse Reactions | N=6,492 [Number with adverse reaction forms] | N=6,484
Mood changes | 11.6 | 10.8
Infection/sepsis | 6.0 | 5.1
Constipation | 4.4 | 3.2
Skin changes | 5.6 | 4.7
Alopecia | 5.2 | 4.4
Allergy | 2.5 | 2.1

In the NSABP P-1 trial, 15.0% and 9.7% of participants receiving tamoxifen and placebo therapy, respectively, withdrew from the trial for medical reasons including the following: hot flashes (3.1% vs. 1.5%, respectively) and vaginal discharge (0.5% vs. 0.1% respectively).

Severe hot flashes occurred in 28% of women on placebo and 45% of women on tamoxifen. Vaginal discharge was severe in 4.5% on placebo and 12.3% on tamoxifen.

SOLTAMOX-related Adverse Reactions

In a single-dose pharmacokinetic study in healthy perimenopausal and postmenopausal women, throat irritation was reported by 3 of 60 evaluable subjects (5%) in the SOLTAMOX treatment group while none of the subjects in the tamoxifen citrate tablet group reported this event. All cases were mild, occurred within an hour after dosing, and resolved within 24 hours.

6.2 Postmarketing Experience

The following adverse reactions have been identified during postapproval use of tamoxifen. Because these reactions are reported voluntarily from a population of uncertain size, it is not always possible to reliably estimate their frequency or establish a causal relationship to drug exposure.

Skin and Subcutaneous Disorders: Erythema multiforme, Stevens-Johnson syndrome, bullous pemphigoid

Respiratory, Thoracic, Mediastinal Disorders: Interstitial pneumonitis

Immune System Disorders: Hypersensitivity reactions including angioedema; in some of these cases, the time to onset was more than one year.

Gastrointestinal Disorders: Elevation of serum triglyceride levels, in some cases with pancreatitis

Men with Metastatic Breast Cancer

Loss of libido and impotence have resulted in discontinuation of tamoxifen therapy in male patients. In oligospermic males treated with tamoxifen, LH, FSH, testosterone, and estrogen levels were elevated, with no reported associated clinical changes.

7 DRUG INTERACTIONS

7.1 Aromatase Inhibitors

Anastrozole

The combination of anastrozole and tamoxifen did not demonstrate any benefit when compared to tamoxifen alone and should be avoided in all patients [see Clinical Studies (14.2)]. In the ATAC trial, coadministration of anastrozole and tamoxifen in breast cancer patients reduced the anastrozole plasma concentration by 27% compared to that achieved with anastrozole alone. The tamoxifen concentration was not altered [see Clinical Pharmacology (12.3)].

Letrozole

The concomitant use of letrozole with tamoxifen is not recommended because the efficacy of the combination in the adjuvant treatment of breast cancer has not been established. Tamoxifen reduced the plasma concentration of letrozole by 38% when these drugs were co-administered [see Clinical Pharmacology (12.3)].

7.2. Warfarin

A marked increase in anticoagulant effect may occur when tamoxifen is used in combination with warfarin. Closely monitor coagulation indices in patients who are taking tamoxifen for either the treatment of metastatic breast cancer or as adjuvant therapy who require concomitant use of warfarin [see Contraindications (4)].

7.3 Inducers of CYP3A4

Strong CYP3A4 inducers should not be used with tamoxifen. Strong CYP3A4 inducers (e.g., rifampin) reduce tamoxifen AUC and Cmax [see Clinical Pharmacology (12.3)].

7.4 Strong Inhibitors of CYP2D6

The impact on the efficacy of tamoxifen with co-administration of strong CYP2D6 inhibitors (e.g., paroxetine) is not well established. Some studies have shown that the efficacy of tamoxifen may be reduced when the drugs are co-administered as a result of reduced levels of potent active metabolites of tamoxifen. However, other studies have failed to demonstrate such an effect [see Clinical Pharmacology (12.3)].

7.5 Drug-Laboratory Test Interactions

There are postmarketing reports of T4 elevations in postmenopausal patients taking tamoxifen that may be explained by increases in thyroid-binding globulin. These elevations were not accompanied by clinical hyperthyroidism.

Variations in the karyopyknotic index on vaginal smears and various degrees of estrogen effect on Pap smears have been seen in postmenopausal patients taking tamoxifen.

8 USE IN SPECIFIC POPULATIONS

8.1 Pregnancy

Risk Summary

SOLTAMOX can cause fetal harm when administered to a pregnant woman. There are no adequate and well- controlled studies of tamoxifen in pregnant women. There are limited postmarketing reports of vaginal bleeding, spontaneous abortions, birth defects, and fetal deaths in pregnant women taking tamoxifen. In a primate model administration of tamoxifen at doses 2 times higher than the maximum recommended human dose resulted in spontaneous abortion. In rat and rabbit studies, doses of tamoxifen less than or equal to human doses resulted in increased embryotoxicity, abortions, and altered learning behaviors. Additionally, rodent models showed reproductive tract changes often associated with DES in offspring of both sexes [see Data]. Advise pregnant women of the potential risk to a fetus, including the potential long-term risk of a DES-like syndrome.

The estimated background risk of major birth defects and miscarriage for the indicated population is unknown. In the U.S. general population, the estimated background risk of major birth defects and miscarriage in clinically recognized pregnancies is 2-4% and 15-20%, respectively.

Data

Animal Data

In embryofetal development studies in rats using doses significantly below those used in humans (0.01 to 0.03 times the recommended human dose on a mg/m^2 basis), a lower incidence of embryo implantation and a higher incidence of fetal death or delayed in utero growth occurred, along with slower learning behavior in some rat pups when compared to historical controls. When pregnant rabbits received tamoxifen during organogenesis, abortion and premature delivery occurred at doses of greater than 0.125 mg/kg/day (about 0.05 times the daily maximum recommended human dose on a mg/m^2 basis). Although reversible nonteratogenic skeletal variations occurred in rat reproductive studies at doses less than or equal to the human dose, there were no teratogenic changes in either rats or rabbits. In pregnant marmosets, administration of 10 mg/kg/day tamoxifen (about 2 times the daily maximum recommended human dose on a mg/m^2 basis) during organogenesis or in the last half of pregnancy terminated pregnancy in some animals. In pregnancies that continued, there were no malformations or deformations in offspring.

In rodent models of fetal reproductive tract development, tamoxifen (at doses 0.002 to 2.4 times the daily maximum recommended human dose on a mg/m^2 basis) caused changes in both sexes that are similar to those caused by estradiol, ethynylestradiol and diethylstilbestrol. Although the clinical relevance of these changes is unknown, some of these changes, especially vaginal adenosis, are similar to those seen in young women who were exposed to diethylstilbestrol in utero and who have a 1 in 1,000 risk of developing clear-cell adenocarcinoma of the vagina or cervix. To date, in utero exposure to tamoxifen has not been shown to cause vaginal adenosis, or clear-cell adenocarcinoma of the vagina or cervix, in young women; however, only a small number of young women have been exposed to tamoxifen in utero, and a smaller number have been followed long enough (to age 15 to 20) to determine whether vaginal or cervical neoplasia could occur as a result of this exposure.

8.2 Lactation

Risk Summary

There is no information regarding the presence of tamoxifen or its metabolites in human milk or its effects on the breastfed infant. Additional information from juvenile animal studies suggests a potential for serious long- term adverse effects for breastfed infants exposed to tamoxifen through breast milk [see Use in Specific Populations (8.4)]. Because of the potential for serious adverse reactions in breastfed infants from tamoxifen, advise a woman not to breastfeed during treatment with SOLTAMOX and for 3 months following the last dose.

Tamoxifen has been reported to inhibit lactation. Two placebo-controlled studies in over 150 women have shown that tamoxifen significantly inhibits early postpartum milk production. In both studies tamoxifen was administered within 24 hours of delivery for between 5 and 18 days. The effect of tamoxifen on established milk production is unknown.

8.3 Females and Males of Reproductive Potential

Pregnancy Testing

A negative pregnancy test should be confirmed in females of reproductive potential before initiation of SOLTAMOX therapy.

Contraception

Females

SOLTAMOX can cause fetal harm. Advise females of reproductive potential to use effective nonhormonal contraception during treatment with SOLTAMOX and for 2 months following the last dose [see Use in Specific Populations (8.1)].

Infertility

Females

Based on animal studies, SOLTAMOX may impair embryo implantation in females of reproductive potential, however, may not reliably cause infertility. Advise women that SOLTAMOX does not always cause infertility, even in the presence of menstrual irregularity [see Nonclinical Toxicology (13.1)].

8.4 Pediatric Use

The safety and effectiveness of SOLTAMOX in pediatric patients have not been established.

Tamoxifen Use in McCune-Albright Syndrome

The safety and effectiveness of SOLTAMOX for the treatment of girls with McCune-Albright syndrome, including long-term effects, have not been established.

A single, uncontrolled multicenter trial of tamoxifen 20 mg once a day was conducted in a heterogeneous group of girls with McCune-Albright syndrome and precocious puberty manifested by physical signs of pubertal development, episodes of vaginal bleeding, and/or advanced bone age (bone age of at least 12 months beyond chronological age). Twenty-eight female pediatric patients, aged 2 to 10 years, were treated for up to 12 months. Effect of treatment on frequency of vaginal bleeding, bone age advancement, and linear growth rate was assessed relative to prestudy baseline. Tamoxifen treatment was associated with a 50% reduction in frequency of vaginal bleeding episodes by patient or family report (mean annualized frequency of 3.56 episodes at baseline and 1.73 episodes on-treatment). Among the patients who reported vaginal bleeding during the prestudy period, 62% (13 out of 21 patients) reported no bleeding for a 6-month period and 33% (7 out of 21 patients) reported no vaginal bleeding for the duration of the trial. Not all patients improved on treatment and a few patients not reporting vaginal bleeding in the 6 months prior to enrollment reported menses on treatment.

Tamoxifen therapy was associated with a reduction in mean rate of increase of bone age (defined as the ratio of bone age change and chronological age); individual responses with regard to this endpoint were highly heterogeneous. Linear growth rate (height velocity) was reduced during the course of tamoxifen treatment in a majority of patients (mean change of 1.68 cm/year relative to baseline; change from 7.47 cm/year at baseline to 5.79 cm/year on study). This change was not uniformly seen across all stages of bone maturity; all recorded response failures occurred in patients with bone ages less than 7 years at screening.

Mean uterine volume increased after 6 months of treatment and doubled at the end of the one-year study. A causal relationship to tamoxifen has not been established; however, as an increase in the incidence of endometrial adenocarcinoma and uterine sarcoma has been noted in adults treated with tamoxifen, continued monitoring of McCune-Albright patients treated with tamoxifen for long-term uterine effects is recommended.

Pharmacokinetics in Pediatric Patients

The pharmacokinetics of tamoxifen and N-desmethyl tamoxifen were characterized using a population pharmacokinetic analysis with sparse samples per patient obtained from 27 female pediatric patients aged 2 to 10 years enrolled in a study of tamoxifen in treating McCune-Albright syndrome. Clearance (CL/F), adjusted for body weight, in female pediatric patients was approximately 2.3-fold higher than in adult female breast cancer patients. In the youngest cohort of female pediatric patients (2 to 6 year olds), CL/F was 2.6-fold higher; in the oldest cohort (7 to 10.9 year olds), CL/F was approximately 1.9-fold higher. Exposure to N-desmethyl tamoxifen was comparable between the pediatric and adult patients.

In pediatric patients, an average steady-state peak plasma concentration (Css, max) and AUC were 187 ng/mL and 4,110 ng hr/mL, respectively, and Css, max occurred approximately 8 hours after dosing.

Animal Data

Direct neonatal exposure of tamoxifen to mice and rats produced: 1) reproductive tract lesions in female rodents (similar to those seen in humans after intrauterine exposure to DES) and 2) functional defects of the reproductive tract in male rodents such as testicular atrophy and arrest of spermatogenesis.

8.5 Geriatric Use

Ductal Carcinoma in Situ

In the NSABP B-24 trial, the percentage of women at least 65 years of age was 23%. Women at least 70 years of age accounted for 10% of participants. A total of 14 and 12 invasive breast cancers were seen among participants 65 and older in the placebo and tamoxifen groups, respectively. This subset is too small to reach any conclusions on efficacy. Across all other endpoints, the results in this subset were comparable to those of younger women enrolled in this trial. No overall differences in tolerability were observed between older and younger patients.

Reduction in Breast Cancer Incidence in Women at High Risk

In the NSABP P-1 trial, the percentage of women at least 65 years of age was 16%. Women at least 70 years of age accounted for 6% of the participants. A reduction in breast cancer incidence was seen among participants in each of the subsets. A total of 28 and 10 invasive breast cancers were seen among participants 65 and older in the placebo and tamoxifen groups, respectively. Across all other outcomes, the results in this subset reflect the results observed in the subset of women at least 50 years of age. No overall differences in tolerability were observed between older and younger patients.

10 OVERDOSAGE

No specific treatment for SOLTAMOX overdosage is recommended, other than symptomatic treatment.

In a study of advanced metastatic cancer patients to determine the maximum tolerated dose of tamoxifen that could reverse multidrug resistance, the following adverse events were observed: acute neurotoxicity manifested by tremor, hyperreflexia, unsteady gait, and dizziness. These symptoms occurred within 3 to 5 days of beginning tamoxifen and cleared within 2 to 5 days after stopping therapy. No permanent neurologic toxicity was noted. One patient experienced a seizure several days after tamoxifen was discontinued and neurotoxic symptoms had resolved. The causal relationship of the seizure to tamoxifen therapy is unknown. Doses given in these patients were all greater than 400 mg/m^2 loading dose (at least 6-fold higher than the recommended dosage), followed by maintenance doses of 150 mg/m^2 of tamoxifen given twice a day (at least 6-fold higher than the recommended dosage).

In the same study, prolongation of the QT interval on the electrocardiogram was noted when patients were given doses higher than 250 mg/m^2 loading dose (at least 6-fold higher than the recommended dose) , followed by maintenance doses of 80 mg/m^2 of tamoxifen given twice a day. For a woman with a body surface area of 1.5 m^2, the minimal loading dose and maintenance doses at which neurological symptoms and QT changes occurred were at least 6-fold higher in respect to the maximum recommended dose.

Signs observed at the highest doses following studies to determine LD50 in animals were respiratory difficulties and convulsions.

11 DESCRIPTION

SOLTAMOX (tamoxifen citrate) oral solution is for oral administration. Tamoxifen citrate is an estrogen agonist/antagonist.

Chemically, tamoxifen is the trans-isomer of a triphenylethylene derivative. The chemical name is (Z)2-[4-(1,2- diphenyl-1-butenyl)phenoxy]-N,N-dimethylethanamine 2-hydroxy-1,2,3- propanetricarboxylate (1:1). The structural formula, empirical formula, and molecular weight are as follows:

C32H37NO8 M.W. 563.62

Tamoxifen citrate has a pKa′ of 8.85. The equilibrium solubility in water at 37°C is 0.5 mg/mL, and is 0.2 mg/mL in 0.02 N HCl at 37°C.

Each 10 mL of SOLTAMOX oral solution contains 20 mg tamoxifen, equivalent to 30.4 mg tamoxifen citrate. The oral solution is a sugar-free, clear colorless liquid, with licorice and aniseed odor and taste supplied in a 150 mL bottle with a dosing cup. SOLTAMOX oral solution contains the following inactive ingredients: ethanol, glycerol, propylene glycol, sorbitol solution, licorice flavor, aniseed flavor, purified water.

12 CLINICAL PHARMACOLOGY

12.1 Mechanism of Action

Tamoxifen is an estrogen agonist/antagonist. Tamoxifen competes with estrogen for binding to the estrogen receptor, which can result in a decrease in estrogen receptor signaling-dependent growth in breast tissue. Tamoxifen has demonstrated antitumor activity against human breast cancer cell lines xenografted in mice. The drug has been shown to inhibit the induction of rat mammary carcinoma induced by dimethylbenzanthracene (DMBA) and to cause the regression of already established DMBA-induced tumors.

12.3 Pharmacokinetics

Absorption and Distribution

Following a single oral dose of 20 mg tamoxifen, an average peak plasma concentration of 40 ng/mL (range 35 to 45 ng/mL) occurred approximately 5 hours after dosing. The decline in plasma concentrations of tamoxifen is biphasic with a terminal elimination half-life of about 5 to 7 days. The average peak plasma concentration of N- desmethyl tamoxifen, the major metabolite, is 15 ng/mL (range 10 to 20 ng/mL). Chronic administration of 10 mg tamoxifen given twice daily for 3 months to patients results in average steady-state plasma concentrations of 120 ng/mL (range 67 to 183 ng/mL) for tamoxifen and 336 ng/mL (range 148 to 654 ng/mL) for N-desmethyl tamoxifen. The average steady-state plasma concentrations of tamoxifen and N-desmethyl tamoxifen after administration of 20 mg tamoxifen once daily for 3 months are 122 ng/mL (range 71 to 183 ng/mL) and 353 ng/mL (range 152 to 706 ng/mL), respectively. The steady-state plasma concentrations of endoxifen and 4-hydroxytamoxifen are 29.1 (95% CI 24.6 to 33.6) and 3.7 (95% CI 3.3 to 4.1) ng/mL, respectively. After initiation of therapy, steady-state concentrations for tamoxifen are achieved in about 4 weeks and steady-state concentrations for N-desmethyl tamoxifen are achieved in about 8 weeks, suggesting a half-life of approximately 14 days for this metabolite. In a steady-state, crossover study of 10 mg tamoxifen tablets given twice a day vs. a 20 mg tamoxifen tablet given once daily, the 20 mg tamoxifen tablet was bioequivalent to the 10 mg tamoxifen tablets.

A pharmacokinetic study was performed in healthy perimenopausal and postmenopausal female subjects to evaluate the bioavailability of SOLTAMOX (n=30) in comparison with the commercially available tamoxifen citrate tablets (n=33) under fasting conditions. A third arm evaluated the effect of food on SOLTAMOX (n=16). The rate and extent of absorption of SOLTAMOX was found to be bioequivalent to that of tamoxifen citrate tablets under fasting conditions. There was no difference in bioavailability (Cmax and AUC) of SOLTAMOX oral solution between fed and fasting states, and therefore SOLTAMOX can be given without regard to meals.

Metabolism

Tamoxifen is extensively metabolized by CYP450 enzymes, including CYP3A, CYP2D6, CYP2C9, CYP2C19, and CYP2B6. N-desmethyltamoxifen, formed predominantly by CYP3A, is the major metabolite found in plasma. The pharmacological activity of N-desmethyltamoxifen is similar to that of tamoxifen. Endoxifen and 4-hydroxytamoxifen, identified as minor metabolites, have 100-fold greater affinity for the estrogen receptor and 30 to 100-fold greater potency in suppressing estrogen-dependent cell proliferation than tamoxifen. The polymorphic enzyme CYP2D6 is involved in the formation of endoxifen and 4-hydroxytamoxifen, and it is the key enzyme that catalyzes the formation of endoxifen from N-desmethyltamoxifen. Endoxifen concentrations may differ among patients because of various CYP2D6 genotypes [see Clinical Pharmacology (12.5)]. Phase 2 enzymes, such as SULT1A1, UGT2B7, and UGT1A4, are associated with tamoxifen clearance from plasma.

Excretion

Studies in women receiving 20 mg of ^14C tamoxifen showed that approximately 65% of the administered dose was excreted from the body over a period of 2 weeks, with fecal excretion as the primary route of elimination. The drug is excreted mainly as polar conjugates, with unchanged drug and unconjugated metabolites accounting for less than 30% of the total fecal radioactivity.

Specific Populations

The effects of age, gender, and race on the pharmacokinetics of tamoxifen in adults have not been determined. Some data are available on tamoxifen pharmacokinetics in children [see Use in Specific Populations (8.4)]. The effects of reduced liver function on the metabolism and pharmacokinetics of tamoxifen have not been determined.

Drug-Drug Interactions

Aromatase Inhibitors

Anastrozole

In the ATAC trial, coadministration of anastrozole and tamoxifen in breast cancer patients reduced the anastrozole plasma concentration by 27% compared to that achieved with anastrozole alone; however, the coadministration did not affect the pharmacokinetics of tamoxifen or N-desmethyltamoxifen [see Clinical Studies (14.2)].

Letrozole

Tamoxifen reduced the plasma concentration of letrozole by 38% when these drugs were coadministered.

CYP P450 3A4 Inducers

Rifampin, a cytochrome P450 3A4 inducer, reduced tamoxifen AUC and Cmax by 86% and 55%, respectively.

CYP2D6 Inhibitors

Although concomitant administration of CYP2D6 inhibitors reduces the plasma concentration of endoxifen, a potent metabolite, the clinical significance is not well established [see Drug Interactions (7.4)]. The mean steady-state endoxifen plasma concentration in patients taking CYP2D6 inhibitors was significantly reduced compared to those not taking concomitant CYP2D6 inhibitors (14.8 ± 10.6 versus 26.7 ± 15.4 ng/mL). The mean steady-state plasma concentration of endoxifen in CYP2D6 normal metabolizers who were not receiving CYP2D6 inhibitors was 31.4 ± 14.7 ng/mL compared to 8.8 ± 3.5 ng/mL in CYP2D6 normal metabolizers receiving potent CYP2D6 inhibitors (e.g., paroxetine, fluoxetine) with tamoxifen. The plasma levels of endoxifen in CYP2D6 normal metabolizers taking potent CYP2D6 inhibitors were similar to the levels observed in CYP2D6 poor metabolizers taking no CYP2D6 inhibitors (8.8 versus 7.2 ng/mL).

Effects of Other Drugs on Tamoxifen

Aminoglutethimide

Aminoglutethimide reduces tamoxifen and N-desmethyl tamoxifen plasma concentrations.

Medroxyprogesterone

Medroxyprogesterone reduces the plasma concentration of N-desmethyl tamoxifen, but not that of tamoxifen.

12.5 Pharmacogenomics

The impact of CYP2D6 polymorphisms on the efficacy of tamoxifen is not well established.

CYP2D6 poor metabolizers carrying two non-functional alleles exhibit significantly lower endoxifen plasma concentrations compared to patients carrying one or more fully functional alleles of CYP2D6.

In patients with estrogen receptor-positive breast cancer who were participating in the WHEL (Women's Health Eating and Living) Study (NCT00003787), the mean (SD) serum concentration of endoxifen was 22.8 (11.3), 15.9 (9.2), 8.1 (4.9) and 5.6 (3.8) ng/mL in 27 ultrarapid, 1,097 normal, 164 intermediate and 82 poor metabolizers (p<0.001), respectively. This finding is consistent with other published studies that report lower endoxifen concentrations in poor metabolizers compared to normal metabolizers.

13 NONCLINICAL TOXICOLOGY

13.1 Carcinogenesis, Mutagenesis, Impairment of Fertility

A carcinogenesis study in rats at doses of 5, 20, and 35 mg/kg/day (approximately 1, 3, and 7× higher than the daily maximum recommended human dose on a mg/m^2 basis) administered by oral gavage for up to 2 years resulted in a significant increase in hepatocellular carcinoma at all doses. The incidence of these tumors was significantly greater among rats administered 20 or 35 mg/kg/day (69%) compared to those administered 5 mg/kg/day (14%). In a separate study, rats were administered tamoxifen at 45 mg/kg/day (approximately 10× the daily maximum recommended human dose on a mg/m^2 basis); hepatocellular neoplasia was exhibited at 3 to 6 months. In addition, granulosa cell ovarian tumors and interstitial cell testicular tumors were observed in two separate mouse studies. The mice were administered the trans and racemic forms of tamoxifen for 13 to 15 months at doses of 5, 20, and 50 mg/kg/day (approximately 0.5, 2, and 5× the daily recommended human dose on a mg/m^2 basis).

Tamoxifen has been found to increase levels of micronucleus formation in vitro in the human lymphoblastoid cell line (MCL-5). No genotoxic potential was found in a conventional battery of in vivo and in vitro assays with prokaryotic and eukaryotic test systems with or without drug metabolizing enzymes; however, increased levels of DNA adducts were observed by ^32P post-labeling in DNA from rat liver and cultured human lymphocytes. Based on these findings, tamoxifen is genotoxic.

Tamoxifen produced impairment of fertility and conception in female rats at doses of 0.04 mg/kg/day (about 0.01-fold the daily maximum recommended human dose on a mg/m^2 basis) when dosed for two weeks prior to mating through day 7 of pregnancy. At this dose, fertility and reproductive indices were markedly reduced with total fetal mortality.

14 CLINICAL STUDIES

14.1 Metastatic Breast Cancer

Premenopausal Women

Three prospective, randomized studies compared another formulation of tamoxifen to ovarian ablation (oophorectomy or ovarian irradiation) in premenopausal women with advanced breast cancer. Although the objective response rate, time to treatment failure, and survival were similar with both treatments, the limited patient accrual prevented a demonstration of equivalence. In an overview analysis of survival data from the 3 studies, the hazard ratio (HR) for death (tamoxifen/ovarian ablation) was 1.00 with two-sided 95% confidence intervals (CI) of 0.73 to 1.37. Limited number of patients with disease progression during tamoxifen therapy responded to subsequent ovarian ablation.

Men with Metastatic Breast Cancer

Published results from 122 patients (119 evaluable) and case reports in 16 patients (13 evaluable) treated with another formulation of tamoxifen have shown that tamoxifen is effective for the palliative treatment of men with metastatic breast cancer. Sixty-six of these 132 evaluable patients responded to tamoxifen, which constitutes a 50% objective response rate.

14.2 Adjuvant Treatment of Breast Cancer

Pooled Studies of Adjuvant Treatment of Breast Cancer

The Early Breast Cancer Trialists' Collaborative Group (EBCTCG) conducted worldwide overviews of systemic adjuvant therapy for early breast cancer in 1985, 1990, 1995, 1998 and 2011.

The 10-year outcome data were reported in 1998 for 36,689 women in 55 randomized trials of another formulation of adjuvant tamoxifen using doses of 20 to 40 mg per day for 1 to 5+ years. Twenty-five percent of patients received 1 year or less of trial treatment, 52% received 2 years, and 23% received about 5 years. Forty-eight percent of tumors were estrogen receptor (ER)- positive (>10 fmol/mg), 21% were ER-poor (<10 fmol/mg), and 31% were ER-unknown. Among 29,441 patients with ER-positive or ER-unknown breast cancer, 58% were entered into trials comparing tamoxifen to no adjuvant therapy and 42% were entered into trials comparing tamoxifen in combination with chemotherapy vs. the same chemotherapy alone. Among these patients, 54% had node-positive disease and 46% had node-negative disease.

In women with ER-positive or ER-unknown breast cancer:

- With positive nodes who received about 5 years of treatment, overall survival at 10 years was 61.4% for tamoxifen vs. 50.5% for control (log-rank 2p <0.00001). The recurrence-free rate at 10 years was 59.7% for tamoxifen vs. 44.5% for control (log-rank 2p <0.00001).
- With negative nodes who received about 5 years of treatment, overall survival at 10 years was 78.9% for tamoxifen vs. 73.3% for control (log-rank 2p <0.00001). The recurrence-free rate at 10 years was 79.2% for tamoxifen vs. 64.3% for control (log-rank 2p <0.00001).
- Who received 1 year or less, 2 years, or about 5 years of tamoxifen, the proportional reductions in mortality were 12%, 17%, and 26%, respectively (2p <0.003). The corresponding reductions in breast cancer recurrence were 21%, 29%, and 47% (2p <0.00001).

Results in patients with ER-poor breast cancer

- Benefit is less clear for women with ER-poor breast cancer in whom the proportional reduction in recurrence was 10% (2p = 0.007) for all durations taken together, or 9% (2p = 0.02) if contralateral breast cancers are excluded. The corresponding reduction in mortality was 6% (not significant).

The effects of about 5 years of tamoxifen on recurrence and mortality were similar regardless of age and concurrent chemotherapy.

The 15-year outcome data were reported in 2011 for 21,457 women in 20 randomized trials, and continued to confirm the earlier overview results. Five-year treatment with adjuvant tamoxifen reduced the 15-year risks of breast cancer recurrence and death.

Node-positive: Individual Studies

Two studies [Hubay and National Surgical Adjuvant Breast and Bowel Project (NSABP) B-09] demonstrated an improved disease-free survival following radical or modified radical mastectomy in postmenopausal women or women 50 years of age or older with surgically curable breast cancer with positive axillary nodes when another formulation of tamoxifen was added to adjuvant cytotoxic chemotherapy. In the Hubay study, tamoxifen was added to "low-dose" CMF (cyclophosphamide, methotrexate, and fluorouracil). In the NSABP B-09 study, tamoxifen was added to melphalan and fluorouracil.

In the Hubay study, patients with a positive (more than 3 fmol) estrogen receptor were more likely to benefit. In the NSABP B-09 study in women age 50 to 59 years, only women with both estrogen and progesterone receptor levels 10 fmol or greater clearly benefited, while survival results were poorer in women with both estrogen and progesterone receptor levels less than 10 fmol. In women age 60 to 70 years, there was an improvement in disease-free survival with tamoxifen without any clear relationship to estrogen or progesterone receptor status.

Three prospective studies (ECOG-1178, Toronto, and Tamoxifen Adjuvant Trial Organization (NATO)] using another formulation of tamoxifen adjuvantly as a single agent demonstrated improved disease-free survival following total mastectomy and axillary dissection for postmenopausal women with positive axillary nodes compared to placebo/no treatment controls. The NATO study also demonstrated an overall survival benefit.

Node–negative: Individual Studies

NSABP B-14, a prospective, double-blind, randomized study, compared another formulation of tamoxifen to placebo as adjuvant therapy in women with axillary node-negative, estrogen-receptor positive (≥10 fmol/mg cytosol protein) breast cancer (following total mastectomy and axillary dissection, or segmental resection, axillary dissection, and breast radiation). After five years of treatment, there was a significant improvement in disease-free survival in women receiving tamoxifen. This benefit was apparent both in women under age 50 and in women at or beyond age 50.

One additional randomized study (NATO) demonstrated improved disease-free survival for another formulation of tamoxifen compared to no adjuvant therapy following total mastectomy and axillary dissection in postmenopausal women with axillary node-negative breast cancer. In this study, the benefits of tamoxifen appeared to be independent of estrogen receptor status.

Duration of Therapy

Available data supported 5 years of adjuvant tamoxifen therapy for patients with breast cancer. In the EBCTCG 1995 overview, the reduction in recurrence and mortality was greater in those studies that used tamoxifen for about 5 years than in those that used tamoxifen for a shorter period of therapy. Although results of the NSABP B-14 study suggest that continuation of therapy beyond five years does not provide additional benefit, a subsequent report of the ATLAS trial suggest that continuing tamoxifen to 10 years further reduced recurrence and mortality.

5 Years vs. Shorter Duration

In the EBCTCG 1995 overview, the reduction in recurrence and mortality was greater in those studies that used tamoxifen for about 5 years than in those that used tamoxifen for a shorter period of therapy.

In a Swedish Breast Cancer Cooperative Group trial of another formulation of adjuvant tamoxifen 40 mg per day (two times the recommended dosage) for 2 or 5 years, overall survival at 10 years was estimated to be 80% in the patients in the 5 year tamoxifen group, compared with 74% among corresponding patients in the 2 year treatment group (p = 0.03). Disease-free survival at 10 years was 73% in the 5 year group and 67% in the 2 year group (p = 0.009). Compared with 2 years of tamoxifen treatment, 5 years of treatment resulted in a slightly greater reduction in the incidence of contralateral breast cancer at 10 years, but this difference was not statistically significant.

5 Years vs. Longer Duration

In the ATLAS trial (Adjuvant Tamoxifen: Longer Against Shorter), 6,846 women with early breast cancer and ER-positive disease who had completed 5 years of treatment with another formulation of tamoxifen were randomly allocated to continue tamoxifen to 10 years or to stop at 5 years. The cumulative risk of recurrence for women randomized to continue tamoxifen was reduced during years 5-9 [recurrence rate ratio of 0.90 (95% CI: 0.79, 1.02)] and further reduced in later years [0.75 (95% CI: 0.62, 0.90)]. Breast cancer mortality in women who received tamoxifen for up to 10 years was also reduced by about 13% [HR = 0.87 (95% CI 0.78, 0.97)].

In the NSABP B-14 trial, in which patients were randomized to another formulation of tamoxifen 20 mg per day for 5 years vs. placebo, those who were disease-free at the end of this 5 year period were offered rerandomization to an additional 5 years of tamoxifen or placebo. With 4 years of follow-up after this rerandomization, 92% of the women that received 5 years of tamoxifen were alive and disease-free, compared to 86% of the women scheduled to receive 10 years of tamoxifen (p = 0.003). Overall survivals were 96% and 94%, respectively (p = 0.08). Results of the B-14 study suggest that continuation of tamoxifen beyond 5 years does not provide additional benefit.

A Scottish trial of 5 years of another formulation of tamoxifen vs. indefinite treatment found a disease-free survival of 70% in the five-year group and 61% in the indefinite group, with 6.2 years median follow-up (HR = 1.27, 95% CI: 0.87 to 1.85).

Contralateral Breast Cancer

The incidence of contralateral breast cancer was reduced in breast cancer patients (premenopausal and postmenopausal) receiving adjuvant tamoxifen compared to placebo. Data on contralateral breast cancer are available from 32,422 out of 36,689 patients in the 1995 overview analysis of the EBCTCG. In clinical trials with tamoxifen of 1 year or less, 2 years, and about 5 years duration, the proportional reductions in the incidence rate of contralateral breast cancer among women receiving tamoxifen were 13% (not significant), 26% (2p = 0.004) and 47% (2p <0.00001), respectively. The reduction in the incidence of contralateral breast cancer was significant with longer tamoxifen duration (2p = 0.008). The proportional reductions in the incidence of contralateral breast cancer were independent of age and ER status of the primary tumor. Treatment with about 5 years of tamoxifen reduced the annual incidence rate of contralateral breast cancer from 7.6 per 1,000 patients in the control group to 3.9 per 1,000 patients in the tamoxifen group.

In a Swedish Breast Cancer Cooperative Group trial where another formulation of adjuvant tamoxifen was given at a dose of 40 mg per day (two times the recommended dosage) for 2 to 5 years, the incidence of second primary breast tumors was reduced 40% (p <0.008) on tamoxifen compared to control. In the NSABP B-14 trial in which patients were randomized to tamoxifen 20 mg per day for 5 years vs. placebo, the incidence of second primary breast cancers was also significantly reduced (p <0.01). The annual rate of contralateral breast cancer was 8.0 per 1,000 patients in the placebo group compared to 5.0 per 1,000 patients in the tamoxifen group, at 10 years after first randomization.

Anastrozole Adjuvant Trial (ATAC: Arimidex, Tamoxifen, Alone or in Combination) – Study of Anastrozole Compared to Tamoxifen for Adjuvant Treatment of Early Breast Cancer

A trial was conducted in 9,366 postmenopausal women with operable breast cancer who were randomized to receive adjuvant treatment with either anastrozole 1 mg daily, another formulation of tamoxifen 20 mg daily, or a combination of these two treatments for 5 years or until recurrence of the disease. At a median follow-up of 33 months, the combination of anastrozole and tamoxifen did not demonstrate any efficacy benefit when compared to tamoxifen alone in all patients, as well as in the hormone receptor-positive subpopulation. The combination treatment arm was discontinued from the trial [see Drug Interactions (7.1) and Clinical Pharmacology (12.3)]. Refer to the full prescribing information for anastrozole tablets for additional information on this trial.

14.3 Ductal Carcinoma in Situ

NSABP B-24 was a double-blind, randomized trial in women with DCIS that compared the addition of another formulation of tamoxifen or placebo to treatment with lumpectomy and radiation therapy. The primary objective was to determine whether 5 years of tamoxifen therapy (20 mg per day) reduced the incidence of invasive breast cancer in the ipsilateral or contralateral breast. In this trial, 1,804 women were randomized to receive either tamoxifen or placebo for 5 years: 902 women were randomized to tamoxifen 10 mg tablets twice a day and 902 women were randomized to placebo. Follow-up data were available for 1,798 women and the median duration of follow-up was 74 months.

The tamoxifen and placebo groups were balanced for baseline demographic and prognostic factors. Over 80% of the tumors were less than or equal to 1 cm in their maximum dimension, were not palpable, and were detected by mammography alone. Over 60% of the study population was postmenopausal. In 16% of patients, the margin of the resected specimen was reported as being positive after surgery. Approximately half of the tumors were reported to contain comedo necrosis.

The incidence of invasive breast cancer was reduced by 43% among women assigned to tamoxifen (44 cases on tamoxifen, 74 cases on placebo; p = 0.004; RR = 0.57, 95% CI: 0.39 to 0.84). No data are available regarding the ER status of the invasive cancers. The stage distribution of the invasive cancers at diagnosis was similar to that reported annually in the SEER data base.

Results are shown in Table 6. At 5 years from study entry, survival was similar in the placebo and tamoxifen groups.

Table 6: Major Outcomes of the NSABP B-24 Trial in Women with DCIS
Type of Event | Lumpectomy, Radiotherapy, and Placebo N=902 |  | Lumpectomy, Radiotherapy, and Tamoxifen N=902 |  | RR | 95% CI
 | No. of events | Rate per 1,000 women per year | No. of events | Rate per 1,000 women per year | RR | 95% CI
Invasive Breast Cancer (Primary Endpoint) | 74 | 16.73 | 44 | 9.60 | 0.57 | 0.39 to 0.84
Ipsilateral | 47 | 10.61 | 27 | 5.90 | 0.56 | 0
Contralateral | 25 | 5.64 | 17 | 3.71 | 0.66 | 0
Side undetermined | 2 | -- | 0 | -- | --
Secondary Endpoints
DCIS | 56 | 12.66 | 41 | 8.95 | 0.71 | 0
Ipsilateral | 46 | 10.40 | 38 | 8.29 | 0.88 | 0
Contralateral | 10 | 2.26 | 3 | 0.65 | 0.29 | 0
All breast cancer events | 129 | 29.16 | 84 | 18.34 | 0.63 | 0
All ipsilateral events | 96 | 21.70 | 65 | 14.19 | 0.65 | 0
All contralateral events | 37 | 8.36 | 20 | 4.37 | 0.52 | 0
Deaths | 32 |  | 28
Uterine malignancies [Updated follow-up data (median 8.1 years)] | 4 |  | 9
Endometrial adenocarcinoma | 4 | 0.57 | 8 | 1.15
Uterine sarcoma | 0 | 0 | 1 | 0.14
Second primary malignancies (other than endometrial and breast) | 30 |  | 29
Stroke | 2 |  | 7
Thromboembolic events (DVT, PE) | 5 |  | 15

14.4 Reduction in Breast Cancer Incidence in Women at High Risk

Breast Cancer Prevention Trial (NSABP P-1)

The Breast Cancer Prevention Trial (NSABP P-1) was a double-blind, randomized, placebo-controlled trial with a primary objective to determine whether 5 years of another formulation of tamoxifen therapy (20 mg per day) reduced the incidence of invasive breast cancer in women at high risk for the disease. Secondary objectives included an evaluation of the incidence of ischemic heart disease; the effects on the incidence of bone fractures; and other events associated with the use of tamoxifen, including endometrial cancer, pulmonary embolus, deep vein thrombosis, stroke, and cataract formation and surgery.

The Breast Cancer Assessment Tool^1 (the Gail Model) was used to calculate predicted breast cancer risk for women who were less than 60 years of age and did not have lobular carcinoma in situ (LCIS). The following risk factors were used: age; number of first-degree female relatives with breast cancer; previous breast biopsies; presence or absence of atypical hyperplasia; nulliparity; age at first live birth; and age at menarche. A 5-year predicted risk of breast cancer of ≥1.67% was required for entry into the trial.

In this trial, 13,388 women of at least 35 years of age were randomized to receive either tamoxifen or placebo for five years. The median duration of treatment was 3.5 years. Follow-up data were available for 13,114 women. Twenty-seven percent of women randomized to placebo (1,782) and 24% of women randomized to tamoxifen (1,596) completed 5 years of therapy.

Demographics

The demographic characteristics of women on the trial with follow-up data are shown in Table 7.

Table 7: Demographic Characteristics of Women in the NSABP P-1 Trial in Women at High Risk for Breast Cancer
Characteristic | Placebo N=6,570 |  | Tamoxifen N=6,544
 | # | % | # | %
Age (yrs.)
35 to 39 | 184 | 3 | 158 | 2
40 to 49 | 2,394 | 36 | 2,411 | 37
50 to 59 | 2,011 | 31 | 2,019 | 31
60 to 69 | 1,588 | 24 | 1,563 | 24
≥70 | 393 | 6 | 393 | 6
Age at first live birth (yrs.)
Nulliparous | 1,202 | 18 | 1,205 | 18
12 to 19 | 915 | 14 | 946 | 15
20 to 24 | 2,448 | 37 | 2,449 | 37
25 to 29 | 1,399 | 21 | 1,367 | 21
≥30 | 606 | 9 | 577 | 9
Race
White | 6,333 | 96 | 6,323 | 96
Black | 109 | 2 | 103 | 2
Other | 128 | 2 | 118 | 2
Age at menarche
≥14 | 1,243 | 19 | 1,170 | 18
12 to 13 | 3,610 | 55 | 3,610 | 55
≤11 | 1,717 | 26 | 1,764 | 27
# of first degree relatives with breast cancer
0 | 1,584 | 24 | 1,525 | 23
1 | 3,714 | 57 | 3,744 | 57
2+ | 1,272 | 19 | 1,275 | 20
Prior hysterectomy
No | 4,173 | 63.5 | 4,018 | 62.4
Yes | 2,397 | 36.5 | 2,464 | 37.7
# of previous breast biopsies
0 | 2,935 | 45 | 2,923 | 45
1 | 1,833 | 28 | 1,850 | 28
≥2 | 1,802 | 27 | 1,771 | 27
History of atypical hyperplasia in the breast
No | 5,958 | 91 | 5,969 | 91
Yes | 612 | 9 | 575 | 9
History of LCIS at entry
No | 6,165 | 94 | 6,135 | 94
Yes | 405 | 6 | 409 | 6
5-year predicted breast cancer risk (%) [As calculated by the Breast Cancer Assessment Tool]
≤2.00 | 1,646 | 25 | 1,626 | 25
2.01 to 3.00 | 2,028 | 31 | 2,057 | 31
3.01 to 5.00 | 1,787 | 27 | 1,707 | 26
≥5.01 | 1,109 | 17 | 1,162 | 18

Results

Results are shown in Table 8. After a median follow-up of 4.2 years, the incidence of invasive breast cancer was reduced by 44% among women assigned to tamoxifen (86 cases on tamoxifen, 156 cases on placebo; p <0.00001; RR = 0.56, 95% CI: 0.43 to 0.72). A reduction in the incidence of breast cancer was seen in each prospectively specified age group (≤49, 50-59, ≥60), in women with or without LCIS, and in each of the absolute risk levels specified in Table 8. A non-significant decrease in the incidence of DCIS was seen (23 tamoxifen, 35 placebo; RR = 0.66, 95% CI: 0.39 to 1.11).

There was no statistically significant difference in the number of myocardial infarctions, severe angina, or acute ischemic cardiac events between the two groups (61 tamoxifen, 59 placebo; RR = 1.04, 95% CI: 0.73 to 1.49).

No overall difference in mortality (53 deaths in tamoxifen group vs. 65 deaths in placebo group) was present. No difference in breast cancer-related mortality was observed (4 deaths in tamoxifen group vs. 5 deaths in placebo group).

Although there was a non-significant reduction in the number of hip fractures (9 on tamoxifen, 20 on placebo) in the tamoxifen group, the number of wrist fractures was similar in the two treatment groups (69 on tamoxifen, 74 on placebo). A subgroup analysis of the trial suggested a difference in effect on bone mineral density (BMD) related to menopausal status in patients receiving tamoxifen. In postmenopausal women, there was no evidence of bone loss of the lumbar spine and hip. Conversely, tamoxifen was associated with significant bone loss of the lumbar spine and hip in premenopausal women.

Tamoxifen increased the risk for endometrial cancer, DVT, PE, stroke, cataract formation, and cataract surgery (see Table 8).

Table 8 summarizes the major outcomes of the NSABP P-1 trial. For most participants, multiple risk factors would have been required for eligibility. This table considers risk factors individually, regardless of other co- existing risk factors, for women who developed breast cancer. The 5-year predicted absolute breast cancer risk accounts for multiple risk factors in an individual and should provide the best estimate of individual benefit.

Table 8: Major Outcomes of the NSABP P-1 Trial in Women at High Risk for Breast Cancer
Type of Event | # of events |  | Rate per 1,000 Women per Year |  | RR | 95% CI
Type of Event | Placebo | Tamoxifen | Placebo | Tamoxifen | RR | 95% CI
Invasive Breast Cancer | 156 | 86 | 6.49 | 3.58 | 0.56 | 0.43 to 0.72
5-year predicted breast cancer risk (as calculated by the Breast Cancer Assessment Tool)
≤2.00% | 31 | 13 | 5.36 | 2.26 | 0.42 | 0.22 to 0.81
2.01 to 3.00% | 39 | 28 | 5.25 | 3.83 | 0.73 | 0.45 to 1.18
3.01 to 5.00% | 36 | 26 | 5.37 | 4.06 | 0.76 | 0.46 to 1.26
≥5.00% | 50 | 19 | 13.15 | 4.71 | 0.36 | 0.21 to 0.61
Individual Risk Factors
Age Groups
Age ≤49 | 59 | 38 | 6.34 | 4.11 | 0.65 | 0.43 to 0.98
Age 50 to 59 | 46 | 25 | 6.31 | 3.53 | 0.56 | 0.35 to 0.91
Age ≥60 | 51 | 23 | 7.17 | 3.22 | 0.45 | 0.27 to 0.74
Risk factors for breast cancer history, LCIS
No | 140 | 78 | 6.23 | 3.51 | 0.56 | 0.43 to 0.74
Yes | 16 | 8 | 12.73 | 6.33 | 0.50 | 0.21 to 1.17
History, atypical hyperplasia
No | 138 | 84 | 6.37 | 3.89 | 0.61 | 0.47 to 0.80
Yes | 18 | 2 | 8.69 | 1.05 | 0.12 | 0.03 to 0.52
Number of first degree relatives with breast cancer
0 | 32 | 17 | 5.97 | 3.26 | 0.55 | 0.30 to 0.98
1 | 80 | 45 | 5.81 | 3.31 | 0.57 | 0.40 to 0.82
2 | 35 | 18 | 8.92 | 4.67 | 0.52 | 0.30 to 0.92
≥3 | 9 | 6 | 13.33 | 7.58 | 0.57 | 0.20 to 1.59
DCIS | 35 | 23 | 1.47 | 0.97 | 0.66 | 0.39 to 1.11
Safety Endpoints
Fractures (protocol-specified sites) | 92 ^1 | 76 [Two women had hip and wrist fractures.] | 3.87 | 3.20 | 0.61 | 0.83 to 1.12
Hip | 20 | 9 | 0.84 | 0.38 | 0.45 | 0.18 to 1.04
Wrist [Includes Colles' and other lower radius fractures] | 74 | 69 | 3.11 | 2.91 | 0.93 | 0.67 to 1.29
Total ischemic events | 59 | 61 | 2.47 | 2.57 | 1.04 | 0.71 to 1.51
Myocardial infarction | 27 | 27 | 1.13 | 1.13 | 1.00 | 0.57 to 1.78
Fatal | 8 | 7 | 0.33 | 0.29 | 0.88 | 0.27 to 2.77
Nonfatal | 19 | 20 | 0.79 | 0.84 | 1.06 | 0.54 to 2.09
Angina [Requiring angioplasty or CABG] | 12 | 12 | 0.50 | 0.50 | 1.00 | 0.41 to 2.44
Acute ischemic syndrome [New Q-wave on ECG; no angina or elevation of serum enzymes; or angina requiring hospitalization without surgery] | 20 | 22 | 0.84 | 0.92 | 1.11 | 0.58 to 2.13
Uterine malignancies [Among women who had not undergone hysterectomy. This updated long-term follow-up data (median 6.9 years) from NSABP P-1 study was added after the cut-off for the other information in this table.] | 17 | 57
Endometrial adenocarcinoma | 17 | 53 | 0.71 | 2.20
Uterine sarcoma | 1 | 4 | 0.0 | 0.17
Stroke [Seven cases were fatal: Three in the placebo group and four in the tamoxifen group.] | 24 | 34 | 1.00 | 1.43 | 1.42 | 0.82 to 2.51
Transient ischemic attack | 21 | 18 | 0.88 | 0.75 | 0.86 | 0.43 to 1.70
Pulmonary emboli [Three cases in the tamoxifen group were fatal.] | 6 | 18 | 0.25 | 0.75 | 3.01 | 1.15 to 9.27
Deep vein thrombosis [All but three cases in each group required hospitalization.] | 19 | 30 | 0.79 | 1.26 | 1.59 | 0.86 to 2.98
Cataracts developing on study [Based on women without cataracts at baseline (6,230 placebo; 6,199 tamoxifen)] | 483 | 540 | 22.51 | 25.41 | 1.13 | 1.00 to 1.28
Underwent cataract surgery | 63 | 101 | 2.83 | 4.57 | 1.62 | 1.18 to 2.22
Underwent cataract surgery [All women (6,707 placebo; 6,681 tamoxifen)] | 129 | 201 | 5.44 | 8.56 | 1.58 | 1.26 to 1.97

Table 9 describes the characteristics of the breast cancers in the NSABP P-1 trial in women at high risk for breast cancer. Tamoxifen decreased the incidence of small estrogen receptor-positive tumors, but did not alter the incidence of estrogen receptor-negative tumors or larger tumors.

Table 9: Characteristics of the Breast Cancers in NSABP P-1 Trial
Staging Parameter | Placebo N=156 | Tamoxifen N=86
Tumor size
T1 | 117 | 60
T2 | 28 | 20
T3 | 7 | 3
T4 | 1 | 2
Unknown | 3 | 1
Nodal status
Negative | 103 | 56
1 to 3 positive nodes | 29 | 14
≥4 positive nodes | 10 | 12
Unknown | 14 | 4
Stage
I | 88 | 47
II: node-negative | 15 | 9
II: node-positive | 33 | 22
III | 6 | 4
IV | 2 [One participant presented with a suspicious bone scan but did not have documented metastases. She subsequently died of metastatic breast cancer.] | 1
Unknown | 12 | 3
Estrogen receptor status
Positive | 115 | 38
Negative | 27 | 36
Unknown | 14 | 12

The 7-year follow-up for the NSABP P-1 trial confirmed the initial findings. The cumulative rates of invasive and non-invasive breast cancer were reduced with tamoxifen. The risks of stroke, deep-vein thrombosis, and cataracts and of ischemic heart disease and death were also similar to those initially reported. Risks of pulmonary embolism were lower than in the original report, and risks of endometrial cancer were higher, but these differences were not statistically significant.

Italian Tamoxifen Prevention Trial and the Royal Marsden Trial

Interim results from two additional trials examining the effects of another formulation of tamoxifen in reducing breast cancer incidence are summarized below.

In the Italian Tamoxifen Prevention trial, 5,408 women without any specific risk factors for breast cancer and who had undergone a total hysterectomy were randomized to receive 20 mg tamoxifen or placebo for 5 years. The primary endpoints were occurrence of, and death from, invasive breast cancer. Hormone replacement therapy (HRT) was used in 14% of participants. The trial closed because of the large number of dropouts during the first year of treatment (26%). After 46 months of follow-up, there were 22 breast cancers in women on placebo and 19 in women on tamoxifen. Although no decrease in breast cancer incidence was observed, there was a trend for reduction in breast cancer among women receiving protocol therapy for at least 1 year (19 placebo, 11 tamoxifen). The small numbers of participants, along with the low level of risk in this otherwise healthy group precluded an adequate assessment of the effect of tamoxifen in reducing the incidence of breast cancer. Tamoxifen is not approved for women who are at low risk for breast cancer.

The Royal Marsden Trial (RMT) was also reported as an interim analysis. The RMT was undertaken as a feasibility study of whether larger scale trials could be mounted. Twenty-four hundred and seventy-one women were enrolled, based on a family history of breast cancer. HRT was used in 40% of participants. In this trial, with a 70-month median follow-up, 34 and 36 breast cancers (8 noninvasive, 4 on each arm) were observed among women on tamoxifen and placebo, respectively. Patients in this trial were younger than those in the NSABP P-1 trial and may have been more likely to develop ER-negative tumors, which are unlikely to be reduced in number by tamoxifen therapy. Although women were selected on the basis of family history and were thought to have a high risk of breast cancer, few events occurred, reducing the statistical power of the study. These factors are potential reasons why the RMT may not have provided an adequate assessment of the effectiveness of tamoxifen in reducing the incidence of breast cancer.

In these two trials, an increased number of cases of deep vein thrombosis, pulmonary embolus, stroke, and endometrial cancer were observed on the tamoxifen arm compared to the placebo arm. The frequencies of these events were consistent with the data observed in the NSABP P-1 trial.

15 REFERENCES

^1Cancer.gov [Internet]. Bethesda (MD):National Cancer Institute [updated 2011 May 16]. Available from: http://www.cancer.gov/bcrisktool/.

16 HOW SUPPLIED/STORAGE AND HANDLING

SOLTAMOX oral solution is a sugar-free, clear colorless liquid, with licorice and aniseed odor and taste. It is supplied in a 150 mL bottle with a dosing cup intended for the measurement of SOLTAMOX oral solution only. Each 10 mL of solution contains 20 mg tamoxifen, equivalent to 30.4 mg tamoxifen citrate.

NDC# 51862-682-01

STORAGE AND HANDLING

Store at room temperatures 20° to 25°C (68° - 77°F); excursions permitted between 15° to 30°C (59° - 86°F) [see USP Controlled Room Temperature].

DO NOT freeze or refrigerate.

Store in original packaging in order to protect from light. Discard any unused portion after 3 months of first opening of the bottle.

17 PATIENT COUNSELING INFORMATION

Advise the patient to read the FDA-approved patient labeling (Medication Guide).

Uterine Malignancies

- Inform women that SOLTAMOX increases the risk of uterine malignancies (endometrial carcinoma and uterine sarcoma), including fatal cases. Advise women to promptly inform a healthcare provider if they experience any abnormal gynecological symptoms (e.g., menstrual irregularities, abnormal vaginal bleeding, changes in vaginal discharge, or pelvic pain or pressure.) Advise women receiving or who have previously received tamoxifen to undergo annual gynecological examinations [see Boxed Warning and Warnings and Precautions (5.1)].

Thromboembolic Events

- Inform patients that SOLTAMOX increases the risk of thromboembolic events (deep vein thrombosis, pulmonary embolism, and stroke), including fatal cases. Advise patients to seek medical attention immediately if signs or symptoms of a thromboembolic event occur [see Boxed Warning and Warnings and Precautions (5.2)].

Embryo-Fetal Toxicity

- Advise pregnant women and females of reproductive potential of the potential that exposure during pregnancy or within 2 months prior to conception can result in fetal harm, including the potential long-term risk of a DES-like syndrome. Advise females to inform their healthcare provider of a known or suspected pregnancy [see Warnings and Precautions (5.3) and Use in Specific Populations (8.1)].
- Advise females of reproductive potential to use effective nonhormonal contraception while taking SOLTAMOX and for 2 months after the last dose [see Use in Specific Populations (8.3)].

Lactation

- Advise women not to breastfeed during treatment and for 3 months after the last dose of SOLTAMOX [see Use in Specific Populations (8.2)].

Effects on the Liver

- Inform patients that SOLTAMOX may increase the risk of liver cancer and liver abnormalities [see Warnings and Precautions (5.4)].

Distributed by:
Mayne Pharma
Greenville, NC 27834

Address medical inquiries to: Mayne Pharma 1-844-825-8500.

F8UD1W4JA2

MEDICATION GUIDE SOLTAMOX® (SOL-ta-mox) (tamoxifen citrate) oral solution

Before taking SOLTAMOX, you and your healthcare provider should talk about the possible benefits and risks.

- The benefits and risks are different for women at high risk for breast cancer and women with breast cancer that is only inside the milk ducts (ductal carcinoma in-situ or DCIS) than for women who have been diagnosed with invasive breast cancer.
- For most people who already have invasive breast cancer, the benefits of SOLTAMOX are greater than the risks.
- Talk to your healthcare provider about which risks may affect you.

What is the most important information I should know about SOLTAMOX?

SOLTAMOX can cause serious side effects, including:

- Uterine cancer. Cancer of the lining of the uterus (endometrial adenocarcinoma) or cancer of the body of the uterus (uterine sarcoma) may happen more often in women who take SOLTAMOX and can lead to death. People who take or have taken SOLTAMOX should have a gynecologic exam every year.
  SOLTAMOX can also cause other non-cancer effects on the uterus, including:
  - overgrowth of the lining of the uterus (hyperplasia) and uterine polyps
  - endometriosis
  - fibroids
  - irregular menstrual periods or no menstrual periods (amenorrhea)
  Tell your healthcare provider right away if you get any of the following symptoms during or after treatment with SOLTAMOX:
  - irregular menstrual periods
  - abnormal vaginal bleeding
  - a change in your vaginal discharge
  - pelvic pain or pressure
- Blood clots in your veins or lungs. Blood clots in your veins or lungs may happen more often in people who take SOLTAMOX and can lead to death, especially in people who take SOLTAMOX during their treatment with chemotherapy.
  Tell your healthcare provider right away if you get any of the following symptoms of a blood clot during treatment with SOLTAMOX:
  - sudden chest pain, shortness of breath, or coughing up blood
  - pain, tenderness, or swelling in one or both of your legs
- Stroke. Stroke can cause serious problems and can lead to death. Get medical help right away if you get any of these symptoms of a stroke:
  - sudden weakness, tingling, or numbness of your face, arm or leg, especially on one side of your body
  - sudden confusion, trouble speaking or understanding
  - sudden trouble seeing in one or both eyes
  - sudden trouble walking, dizziness, loss of balance or coordination
  - sudden severe headache with no known cause

What is SOLTAMOX?

SOLTAMOX is a prescription medicine used:

- to treat adults with estrogen receptor-positive breast cancer that has spread to other parts of the body (metastatic)
- to treat adults with early stage estrogen receptor-positive breast cancer after surgery and radiation for breast cancer
- to reduce the chance of developing breast cancer in the other breast in adults after surgery and radiation for breast cancer
- to reduce the risk of invasive breast cancer in adult women with DCIS, after breast surgery and radiation treatment
- to reduce the risk of getting breast cancer in women with a high risk of getting breast cancer

It is not known if SOLTAMOX is safe and effective in children.

Do not take SOLTAMOX if you:

- have had a serious allergic reaction to tamoxifen or any other ingredient in SOLTAMOX. Ask your healthcare provider if you are not sure.
- have DCIS or a high-risk of breast cancer, and you
  - need to take the blood thinner medicine warfarin, or
  - have a history of a blood clot in your veins or lungs

Before taking SOLTAMOX, tell your healthcare provider about all of your medical conditions, including if you:

- have uterine cancer or other problems with your uterus. See "What is the most important information I should know about SOLTAMOX?"
- have irregular menstrual periods, no menstrual periods, or abnormal vaginal bleeding
- have or had a blood clot in your veins or lungs
- have had a stroke
- are pregnant or plan to become pregnant. SOLTAMOX can harm your unborn baby. You should not become pregnant during treatment with SOLTAMOX or within 2 months after you stop taking it.
  Females who are able to become pregnant:
  - Before you start treatment with SOLTAMOX, your healthcare provider should do a pregnancy test to make sure that you are not pregnant.
  - You should use effective birth control (contraception) during treatment with SOLTAMOX and for 2 months after the last dose. Talk to your healthcare provider about birth control options that you may use during this time. You should not use hormonal contraceptives such as birth control pills, patches, implants, or IUDs that contain hormones.
  - Tell your healthcare provider right away if you become pregnant during treatment with SOLTAMOX.
- are breastfeeding or plan to breastfeed. It is not known if SOLTAMOX passes into your breast milk. You should not breastfeed during treatment with SOLTAMOX and for 3 months after the last dose.

Tell your healthcare provider about all the medicines you take, including prescription and over-the-counter medicines, vitamins, and herbal supplements.

Know the medicines you take. Keep a list of them to show to your healthcare provider and pharmacist when you get a new medicine.

How should I take SOLTAMOX?

- Take SOLTAMOX exactly as your healthcare provider tells you to take it.
- Your healthcare provider will tell you how much SOLTAMOX to take and when to take it.
- Your healthcare provider will decide how long you should continue to take SOLTAMOX, depending on your medical condition.
- Do not stop taking SOLTAMOX without first talking with your healthcare provider.
- Use the dosing cup that comes with SOLTAMOX to measure the correct amount for each dose. Ask your healthcare provider or pharmacist if you are not sure how to measure your dose.
- If you forget a dose of SOLTAMOX, take it when you remember, then take the next dose at your usual time. If it is almost time for your next dose, skip the missed dose. Just take the next dose at your regular time. Do not take 2 doses at the same time. If you are not sure about your dosing, call your healthcare provider.
- If you take too much SOLTAMOX, call your healthcare provider right away.

What are the possible side effects of SOLTAMOX?

SOLTAMOX can cause serious side effects, including:

- See "What is the most important information I should know about SOLTAMOX?"
- Liver problems, including liver cancer. SOLTAMOX can cause changes in liver function blood tests, and sometimes can cause liver cancer and other serious liver problems that can lead to death. Your healthcare provider should do blood tests to check you for these problems during treatment with SOLTAMOX.
- Other cancers.
- High levels of calcium in the blood (hypercalcemia). People with breast cancer that has spread to their bones may develop hypercalcemia. Hypercalcemia can happen within a few weeks after you start taking SOLTAMOX. Your healthcare provider should check you for this problem. If it is severe, your healthcare provider may tell you to stop taking SOLTAMOX.
- Decreased blood cell counts. SOLTAMOX can cause a decrease in platelet counts, red blood cell counts, and white blood cell counts that can be severe. Your healthcare provider should check your blood counts during treatment with SOLTAMOX.
- Eye problems. SOLTAMOX can increase your chance of developing cataracts and other eye problems. Tell your healthcare provider about any changes in your vision or other eye symptoms during treatment with SOLTAMOX.

The most common side effects of SOLTAMOX include:

- hot flashes
- mood changes
- vaginal discharge
- vaginal bleeding. See "What is the most important information I should know about SOLTAMOX?"
- nausea
- swelling (fluid retention)

Tell your healthcare provider if you have any side effect that bothers you or that does not go away.

These are not all the possible side effects of SOLTAMOX.

Call your healthcare provider for medical advice about side effects. You may report side effects to FDA at 1-800-FDA-1088.

How should I store SOLTAMOX?

- Store SOLTAMOX at room temperature between 68°F to 77°F (20°C to 25°C). Do not freeze or refrigerate.
- Keep SOLTAMOX in the original bottle to protect it from light.
- Keep the bottle tightly closed.
- Use within 3 months of opening. Throw away any SOLTAMOX remaining in the bottle after 3 months.

Keep SOLTAMOX and all medicines out of the reach of children.

General information about the safe and effective use of SOLTAMOX.

Medicines are sometimes prescribed for purposes other than those listed in a Medication Guide. Do not use SOLTAMOX for a condition for which it was not prescribed. Do not give SOLTAMOX to other people, even if they have the same symptoms that you have. It may harm them. If you would like more information, talk with your healthcare provider. You can ask your pharmacist or healthcare provider for information about SOLTAMOX that is written for health professionals.

What are the ingredients in SOLTAMOX?

Active ingredient: tamoxifen citrate

Inactive ingredients: ethanol, glycerol, propylene glycol, sorbitol solution, licorice flavor, aniseed flavor, purified water.

Distributed by:
Mayne Pharma
Greenville, NC 27834

The brands listed (other than SOLTAMOX®) are registered trademarks of their respective owners.

For more information, call 1-844-825-8500.

This Medication Guide has been approved by the U.S. Food and Drug Administration.

Revised: 11/2020

F8UD1W4JB2

PRINCIPAL DISPLAY PANEL - 150 mL Container Carton

NDC 51862-682-01

SUGAR
FREE

soltamox®
(tamoxifen citrate)
oral solution

equivalent to
20 mg/10 mL
Tamoxifen

Rx only

150 mL